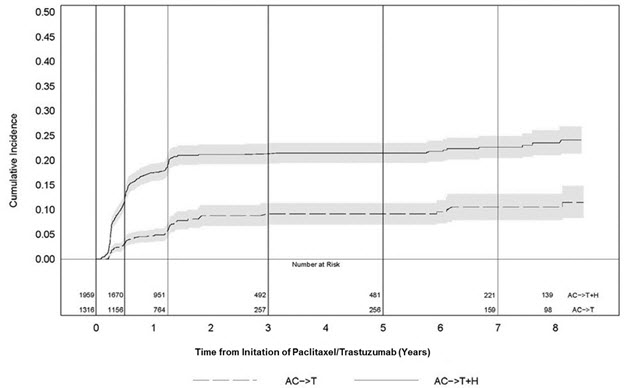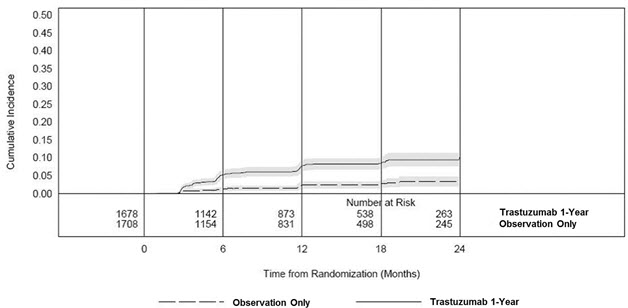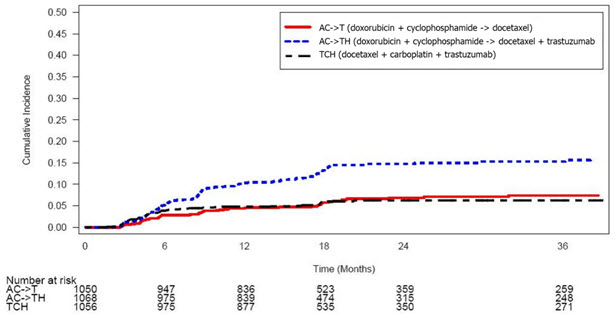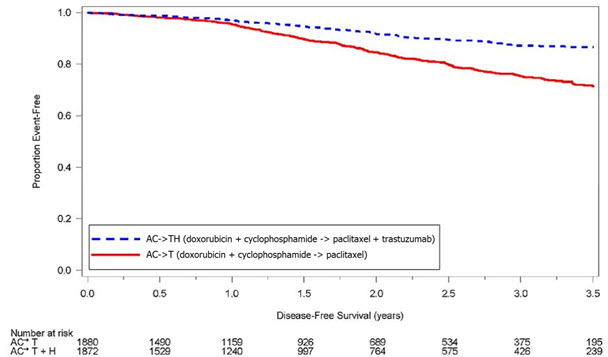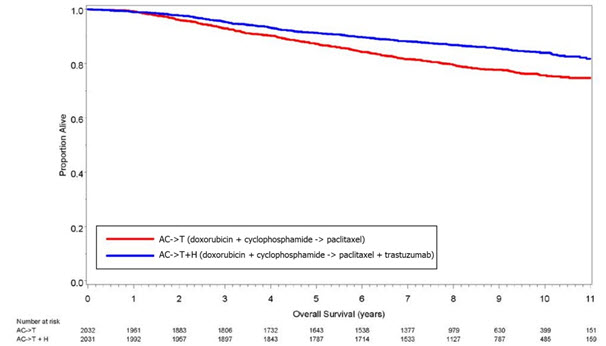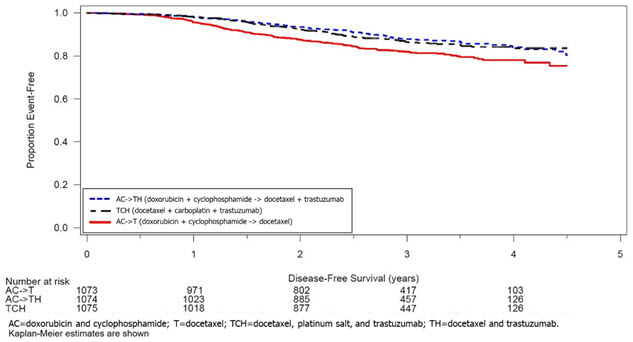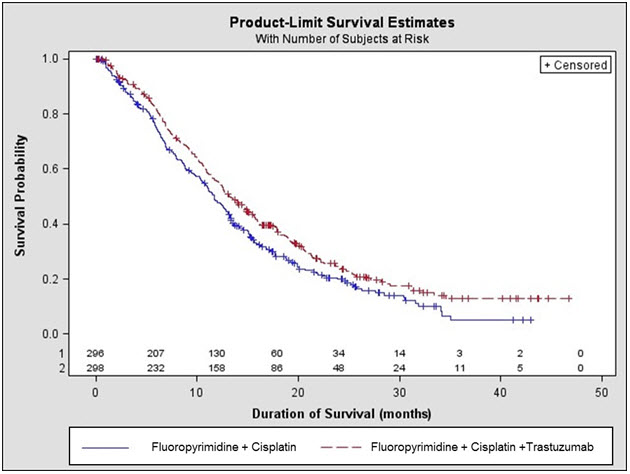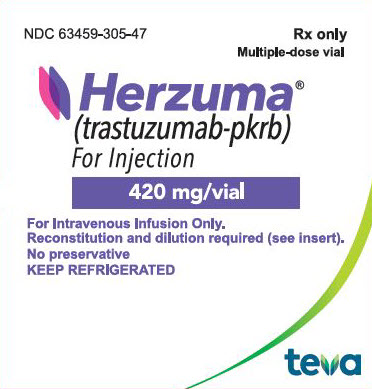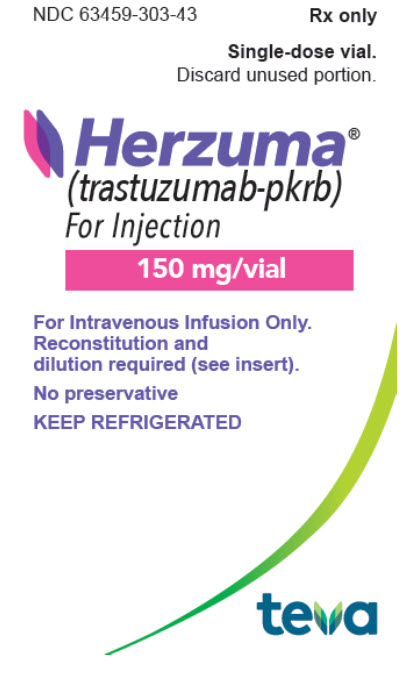 DRUG LABEL: HERZUMA
NDC: 63459-305 | Form: KIT | Route: INTRAVENOUS
Manufacturer: Cephalon, Inc.
Category: prescription | Type: HUMAN PRESCRIPTION DRUG LABEL
Date: 20251222

ACTIVE INGREDIENTS: TRASTUZUMAB 420 mg/20 mL
INACTIVE INGREDIENTS: TREHALOSE DIHYDRATE 839 mg/20 mL; HISTIDINE MONOHYDROCHLORIDE 9.5 mg/20 mL; HISTIDINE 6.1 mg/20 mL; POLYSORBATE 20 1.7 mg/20 mL; BENZYL ALCOHOL 0.22 g/20 mL

HIGHLIGHTS OF PRESCRIBING INFORMATION

These highlights do not include all the information needed to use HERZUMA safely and effectively. See full prescribing information for HERZUMA.
HERZUMA® (trastuzumab-pkrb) for injection, for intravenous use
Initial U.S. Approval: 2018
HERZUMA (trastuzumab-pkrb) is biosimilar [Biosimilar means that the biological product is approved based on data demonstrating that it is highly similar to an FDA-approved biological product, known as a reference product, and that there are no clinically meaningful differences between the biosimilar product and the reference product. Biosimilarity of HERZUMA has been demonstrated for the condition(s) of use (e.g. indication(s), dosing regimen(s)), strength(s), dosage form(s), and route(s) of administration described in its Full Prescribing Information.] to HERCEPTIN (trastuzumab).

WARNING: CARDIOMYOPATHY, INFUSION REACTIONS, EMBRYO-FETAL TOXICITY, and PULMONARY TOXICITY

See full prescribing information for complete boxed warning

Cardiomyopathy: Trastuzumab products can result in subclinical and clinical cardiac failure manifesting as CHF, and decreased LVEF, with greatest risk when administered concurrently with anthracyclines. Evaluate cardiac function prior to and during treatment. Discontinue HERZUMA for cardiomyopathy. (2.5, 5.1)

Infusion Reactions, Pulmonary Toxicity: Discontinue HERZUMA for anaphylaxis, angioedema, interstitial pneumonitis, or acute respiratory distress syndrome. (5.2, 5.4)

Embryo-Fetal Toxicity: Exposure to trastuzumab products during pregnancy can result in oligohydramnios, in some cases complicated by pulmonary hypoplasia and neonatal death. Advise patients of these risks and the need for effective contraception. (5.3, 8.1, 8.3)

RECENT MAJOR CHANGES

Dosage and Administration, Evaluation and Testing Before Initiating HERZUMA (2.1) | 11/2024

1 INDICATIONS AND USAGE

HERZUMA is a HER2/neu receptor antagonist indicated in adults for:

- the treatment of HER2-overexpressing breast cancer. (1.1, 1.2)
- the treatment of HER2-overexpressing metastatic gastric or gastroesophageal junction adenocarcinoma. (1.3)

Select patients for therapy based on an FDA-approved companion diagnostic for a trastuzumab product. (1, 2.2)

2 DOSAGE AND ADMINISTRATION

For intravenous (IV) infusion only. Do not administer as an IV push or bolus. HERZUMA has different dosage and administration instructions than subcutaneous trastuzumab products. (2.3)

Do not substitute HERZUMA (trastuzumab-pkrb) for or with ado-trastuzumab emtansine or fam-trastuzumab deruxtecan. (2.3)

Perform HER2 testing using FDA-approved tests by laboratories with demonstrated proficiency. (1, 2.2)

Adjuvant Treatment of HER2-Overexpressing Breast Cancer (2.2)

Administer at either:

- Initial dose of 4 mg/kg over 90 minutes IV infusion, then 2 mg/kg over 30 minutes IV infusion weekly for 12 weeks (with paclitaxel or docetaxel) or 18 weeks (with docetaxel and carboplatin). One week after the last weekly dose of HERZUMA, administer 6 mg/kg as an IV infusion over 30 to 90 minutes every three weeks to complete a total of 52 weeks of therapy, or
- Initial dose of 8 mg/kg over 90 minutes IV infusion, then 6 mg/kg over 30 to 90 minutes IV infusion every three weeks for 52 weeks.

Metastatic HER2-Overexpressing Breast Cancer (2.3)

- Initial dose of 4 mg/kg as a 90 minutes IV infusion followed by subsequent weekly doses of 2 mg/kg as 30 minutes IV infusions.

Metastatic HER2-Overexpressing Gastric Cancer (2.3)

- Initial dose of 8 mg/kg over 90 minutes IV infusion, followed by 6 mg/kg over 30 to 90 minutes IV infusion every 3 weeks.

3 DOSAGE FORMS AND STRENGTHS

- For Injection: 150 mg lyophilized powder in a single-dose vial for reconstitution. (3)
- For Injection: 420 mg lyophilized powder in a multiple-dose vial for reconstitution. (3)

4 CONTRAINDICATIONS

None. (4)

5 WARNINGS AND PRECAUTIONS

- Exacerbation of Chemotherapy-Induced Neutropenia. (5.5, 6.1)

6 ADVERSE REACTIONS

Adjuvant Breast Cancer

- Most common adverse reactions (≥ 5%) are headache, diarrhea, nausea, and chills. (6.1)

Metastatic Breast Cancer

- Most common adverse reactions (≥ 10%) are fever, chills, headache, infection, congestive heart failure, insomnia, cough, and rash. (6.1)

Metastatic Gastric Cancer

- Most common adverse reactions (≥ 10%) are neutropenia, diarrhea, fatigue, anemia, stomatitis, weight loss, upper respiratory tract infections, fever, thrombocytopenia, mucosal inflammation, nasopharyngitis, and dysgeusia. (6.1)

To report SUSPECTED ADVERSE REACTIONS, contact Teva Pharmaceuticals at 1-888-483-8279 or FDA at 1-800-FDA-1088 or www.fda.gov/medwatch.

8 USE IN SPECIFIC POPULATIONS

Females and Males of Reproductive Potential: Verify the pregnancy status of females prior to initiation of HERZUMA. (8.3)

FULL PRESCRIBING INFORMATION

WARNING: CARDIOMYOPATHY, INFUSION REACTIONS, EMBRYO-FETAL TOXICITY, and PULMONARY TOXICITY

Cardiomyopathy

Administration of trastuzumab products can result in sub-clinical and clinical cardiac failure. The incidence and severity was highest in patients receiving trastuzumab with anthracycline-containing chemotherapy regimens.

Evaluate left ventricular function in all patients prior to and during treatment with HERZUMA. Discontinue HERZUMA treatment in patients receiving adjuvant therapy and withhold HERZUMA in patients with metastatic disease for clinically significant decrease in left ventricular function [see Dosage and Administration (2.5) and Warnings and Precautions (5.1)].

Infusion Reactions; Pulmonary Toxicity

Administration of trastuzumab products can result in serious and fatal infusion reactions and pulmonary toxicity. Symptoms usually occur during or within 24 hours of administration of trastuzumab products. Interrupt HERZUMA infusion for dyspnea or clinically significant hypotension. Monitor patients until symptoms completely resolve. Discontinue HERZUMA for anaphylaxis, angioedema, interstitial pneumonitis, or acute respiratory distress syndrome [see Warnings and Precautions (5.2, 5.4)].

Embryo-Fetal Toxicity

Exposure to trastuzumab products during pregnancy can result in oligohydramnios and oligohydramnios sequence manifesting as pulmonary hypoplasia, skeletal abnormalities, and neonatal death. Advise patients of these risks and the need for effective contraception [see Warnings and Precautions (5.3) and Use in Specific Populations (8.1, 8.3)].

1 INDICATIONS AND USAGE

1.1 Adjuvant Breast Cancer

HERZUMA is indicated in adults for adjuvant treatment of HER2 overexpressing node positive or node negative (ER/PR negative or with one high risk feature [see Clinical Studies (14.1)]) breast cancer

- as part of a treatment regimen consisting of doxorubicin, cyclophosphamide, and either paclitaxel or docetaxel
- as part of a treatment regimen with docetaxel and carboplatin
- as a single agent following multi-modality anthracycline based therapy

Select patients for therapy based on an FDA-approved companion diagnostic for a trastuzumab product [see Dosage and Administration (2.2)].

1.2 Metastatic Breast Cancer

HERZUMA is indicated in adults:

- In combination with paclitaxel for first-line treatment of HER2-overexpressing metastatic breast cancer
- As a single agent for treatment of HER2-overexpressing breast cancer in patients who have received one or more chemotherapy regimens for metastatic disease.

Select patients for therapy based on an FDA-approved companion diagnostic for a trastuzumab product [see Dosage and Administration (2.2)].

1.3 Metastatic Gastric Cancer

HERZUMA is indicated in adults, in combination with cisplatin and capecitabine or 5-fluorouracil, for the treatment of patients with HER2 overexpressing metastatic gastric or gastroesophageal junction adenocarcinoma who have not received prior treatment for metastatic disease.

Select patients for therapy based on an FDA-approved companion diagnostic for a trastuzumab product [see Dosage and Administration (2.2)].

2 DOSAGE AND ADMINISTRATION

2.1 Evaluation and Testing Before Initiating HERZUMA

Assess left ventricular ejection fraction (LVEF) prior to initiation of HERZUMA and at regular intervals during treatment. [see Boxed Warning, Dosage and Administration (2.5), Warnings and Precautions (5.1)].

Verify the pregnancy status of females of reproductive potential prior to the initiation of HERZUMA [see Warnings and Precautions (5.3), Use in Specific Populations (8.1, 8.3)].

2.2 Patient Selection

Select patients based on HER2 protein overexpression or HER2 gene amplification in tumor specimens [see Indications and Usage (1) and Clinical Studies (14)]. Assessment of HER2 protein overexpression and HER2 gene amplification should be performed using FDA-approved tests specific for breast or gastric cancers by laboratories with demonstrated proficiency. Information on the FDA-approved tests for the detection of HER2 protein overexpression and HER2 gene amplification is available at: http://www.fda.gov/CompanionDiagnostics.

Assessment of HER2 protein overexpression and HER2 gene amplification in metastatic gastric cancer should be performed using FDA-approved tests specifically for gastric cancers due to differences in gastric vs. breast histopathology, including incomplete membrane staining and more frequent heterogeneous expression of HER2 seen in gastric cancers.

Improper assay performance, including use of suboptimally fixed tissue, failure to utilize specified reagents, deviation from specific assay instructions, and failure to include appropriate controls for assay validation, can lead to unreliable results.

2.3 Recommended Dosage

- HERZUMA is for intravenous infusion only. Do not administer as an intravenous push or bolus.
- HERZUMA has different dosage and administration instructions than subcutaneous trastuzumab products.
- Do not mix HERZUMA with other drugs.
- Do not substitute HERZUMA (trastuzumab-pkrb) for or with ado-trastuzumab emtansine or fam-trastuzumab deruxtecan.

Adjuvant Treatment of Breast Cancer

Administer according to one of the following doses and schedules for a total of 52 weeks of HERZUMA therapy:

During and following paclitaxel, docetaxel, or docetaxel and carboplatin:

- Initial dose of 4 mg/kg as an intravenous infusion over 90 minutes then at 2 mg/kg as an intravenous infusion over 30 minutes weekly during chemotherapy for the first 12 weeks (paclitaxel or docetaxel) or 18 weeks (docetaxel and carboplatin).
- One week following the last weekly dose of HERZUMA, administer HERZUMA at 6 mg/kg as an intravenous infusion over 30 to 90 minutes every three weeks.

As a single agent within three weeks following completion of multi-modality, anthracycline-based chemotherapy regimens:

- Initial dose at 8 mg/kg as an intravenous infusion over 90 minutes
- Subsequent doses at 6 mg/kg as an intravenous infusion over 30 to 90 minutes every three weeks.
- Extending adjuvant treatment beyond one year is not recommended [see Adverse Reactions (6.1)].

Metastatic Breast Cancer

- Administer HERZUMA, alone or in combination with paclitaxel, at an initial dose of 4 mg/kg as a 90-minute intravenous infusion followed by subsequent once weekly doses of 2 mg/kg as 30-minute intravenous infusions until disease progression.

Metastatic Gastric Cancer

- Administer HERZUMA at an initial dose of 8 mg/kg as a 90-minute intravenous infusion followed by subsequent doses of 6 mg/kg as an intravenous infusion over 30 to 90 minutes every three weeks until disease progression.

2.4 Important Dosing Considerations

Missed Dose

If the patient has missed a dose of HERZUMA by one week or less, then the usual maintenance dose (weekly schedule: 2 mg/kg; once every three week schedule: 6 mg/kg) should be administered as soon as possible. Do not wait until the next planned cycle. Subsequent HERZUMA maintenance doses should be administered 7 days or 21 days later according to the weekly or once every three week schedules, respectively.

If the patient has missed a dose of HERZUMA by more than one week, a re-loading dose of HERZUMA should be administered over approximately 90 minutes (weekly schedule: 4 mg/kg; once every three week schedule: 8 mg/kg) as soon as possible. Subsequent HERZUMA maintenance doses (weekly schedule: 2 mg/kg; once every three week schedule 6 mg/kg) should be administered 7 days or 21 days later according to the weekly or once every three week schedules, respectively.

2.5 Dosage Modifications for Adverse Reactions

Infusion Reactions

[see Boxed Warning, Warnings and Precautions (5.2)]

- Decrease the rate of infusion for mild or moderate infusion reactions
- Interrupt the infusion in patients with dyspnea or clinically significant hypotension
- Discontinue HERZUMA for severe or life-threatening infusion reactions.

Cardiomyopathy

[see Boxed Warning, Warnings and Precautions (5.1)]

Assess left ventricular ejection fraction (LVEF) prior to initiation of HERZUMA and at regular intervals during treatment. Withhold HERZUMA dosing for at least 4 weeks for either of the following:

- ≥ 16% absolute decrease in LVEF from pre-treatment values
- LVEF below institutional limits of normal and ≥ 10% absolute decrease in LVEF from pretreatment values.

HERZUMA may be resumed if, within 4 to 8 weeks, the LVEF returns to normal limits and the absolute decrease from baseline is ≤ 15%.

Permanently discontinue HERZUMA for a persistent (> 8 weeks) LVEF decline or for suspension of HERZUMA dosing on more than 3 occasions for cardiomyopathy.

2.6 Preparation Instructions

To prevent medication errors, it is important to check the vial labels to ensure that the drug being prepared and administered is HERZUMA (trastuzumab-pkrb) and not ado-trastuzumab emtansine or fam-trastuzumab deruxtecan.

420 mg Multiple-dose vial

Reconstitution

Reconstitute each 420 mg vial of HERZUMA with 20 mL of Bacteriostatic Water for Injection (BWFI), USP, containing 1.1% benzyl alcohol as a preservative to yield a multiple-dose solution containing 21 mg/mL trastuzumab-pkrb that delivers 20 mL (420 mg trastuzumab-pkrb). In patients with known hypersensitivity to benzyl alcohol, reconstitute with 20 mL of Sterile Water for Injection (SWFI) without preservative to yield a one-time use solution.

Use appropriate aseptic technique when performing the following reconstitution steps:

- Using a sterile syringe, slowly inject the 20 mL of diluent into the vial containing the lyophilized powder of HERZUMA, which has a cake-like appearance. The stream of diluent should be directed into the cake. The reconstituted vial yields a solution for multiple-dose use, containing 21 mg/mL trastuzumab-pkrb.
- Swirl the vial gently to aid reconstitution. DO NOT SHAKE.
- Slight foaming of the product may be present upon reconstitution. Allow the vial to stand undisturbed for approximately 5 minutes.
- Parenteral drug products should be inspected visually for particulate matter and discoloration prior to administration, whenever solution and container permit. Inspect visually for particulates and discoloration. The solution should be free of visible particulates, clear to slightly opalescent and colorless to pale yellow.
- Store reconstituted HERZUMA in the refrigerator at 2°C to 8°C (36°F to 46°F); discard unused HERZUMA after 28 days. If HERZUMA is reconstituted with SWFI without preservative, use immediately and discard any unused portion. Do not freeze.

Dilution

- Determine the dose (mg) of HERZUMA [see Dosage and Administration (2.3)]. Calculate the volume of the 21 mg/mL reconstituted HERZUMA solution needed, withdraw this amount from the vial using a sterile needle and syringe and add it to an infusion bag containing 250 mL of 0.9% Sodium Chloride Injection, USP. DO NOT USE DEXTROSE (5%) SOLUTION.
- Gently invert the bag to mix the solution.
- The solution of HERZUMA for infusion diluted in polyvinylchloride or polyethylene bags containing 0.9% Sodium Chloride Injection, USP, should be stored at 2°C to 8°C (36°F to 46°F) for no more than 24 hours prior to use. This storage time is additional to the time allowed for the reconstituted vials. Do not freeze.

150 mg Single-dose vial

Reconstitution

Reconstitute each 150 mg vial of HERZUMA with 7.4 mL of Sterile Water for Injection (SWFI) (not supplied) to yield a single-dose solution containing 21 mg/mL trastuzumab-pkrb that delivers 7.15 mL (150 mg trastuzumab-pkrb).

Use appropriate aseptic technique when performing the following reconstitution steps:

- Using a sterile syringe, slowly inject 7.4 mL of SWFI (not supplied) into the vial containing the lyophilized powder of HERZUMA, which has a cake-like appearance. The stream of diluent should be directed into the cake. The reconstituted vial yields a solution containing 21 mg/mL trastuzumab-pkrb.
- Swirl the vial gently to aid reconstitution. DO NOT SHAKE.
- Slight foaming of the product may be present upon reconstitution. Allow the vial to stand undisturbed for approximately 5 minutes.
- Parenteral drug products should be inspected visually for particulate matter and discoloration prior to administration, whenever solution and container permit. Inspect visually for particulates and discoloration. The solution should be free of visible particulates, clear to slightly opalescent and colorless to pale yellow.
- Use the HERZUMA solution immediately following reconstitution with SWFI, as it contains no preservative and is intended for one-time use only. If not used immediately, store the reconstituted HERZUMA solution for up to 24 hours at 2°C to 8°C (36°F to 46°F); discard any unused HERZUMA after 24 hours. Do not freeze.

Dilution

- Determine the dose (mg) of HERZUMA [see Dosage and Administration (2.3)].
- Calculate the volume of the 21 mg/mL reconstituted HERZUMA solution needed.
- Withdraw this amount from the vial using a sterile needle and syringe and add it to an infusion bag containing 250 mL of 0.9% Sodium Chloride Injection, USP. DO NOT USE DEXTROSE (5%) SOLUTION.
- Gently invert the bag to mix the solution.
- The solution of HERZUMA for infusion diluted in polyvinylchloride or polyethylene bags containing 0.9% Sodium Chloride Injection, USP, should be stored at 2°C to 8°C (36°F to 46°F) for no more than 24 hours prior to use. Discard after 24 hours. This storage time is additional to the time allowed for the reconstituted vials. Do not freeze.

3 DOSAGE FORMS AND STRENGTHS

- For injection: 150 mg of HERZUMA as a white to pale yellow lyophilized powder in a single-dose vial
- For injection: 420 mg of HERZUMA as a white to pale yellow lyophilized powder in a multiple-dose vial.

4 CONTRAINDICATIONS

None.

5 WARNINGS AND PRECAUTIONS

5.1 Cardiomyopathy

Trastuzumab products can cause left ventricular cardiac dysfunction, arrhythmias, hypertension, disabling cardiac failure, cardiomyopathy, and cardiac death [see Boxed Warning: Cardiomyopathy]. Trastuzumab products can also cause asymptomatic decline in left ventricular ejection fraction (LVEF).

There is a 4 to 6 fold increase in the incidence of symptomatic myocardial dysfunction among patients receiving trastuzumab products as a single agent or in combination therapy compared with those not receiving trastuzumab products. The highest absolute incidence occurs when a trastuzumab product is administered with an anthracycline.

Withhold HERZUMA for ≥ 16% absolute decrease in LVEF from pre-treatment values or an LVEF value below institutional limits of normal and ≥ 10% absolute decrease in LVEF from pretreatment values [see Dosage and Administration (2.5)]. The safety of continuation or resumption of trastuzumab products in patients with trastuzumab product-induced left ventricular cardiac dysfunction has not been studied.

Patients who receive anthracycline after stopping trastuzumab products may also be at increased risk of cardiac dysfunction [see Drug Interactions (7) and Clinical Pharmacology (12.3)].

Cardiac Monitoring

Conduct thorough cardiac assessment, including history, physical examination, and determination of LVEF by echocardiogram or MUGA scan. The following schedule is recommended:

- Baseline LVEF measurement immediately prior to initiation of HERZUMA
- LVEF measurements every 3 months during and upon completion of HERZUMA
- Repeat LVEF measurement at 4 week intervals if HERZUMA is withheld for significant left ventricular cardiac dysfunction [see Dosage and Administration (2.5)]
- LVEF measurements every 6 months for at least 2 years following completion of HERZUMA as a component of adjuvant therapy.

In NSABP B31, 15% (158/1031) of patients discontinued trastuzumab due to clinical evidence of myocardial dysfunction or significant decline in LVEF after a median follow-up duration of 8.7 years in the AC-TH (anthracycline, cyclophosphamide, paclitaxel, and trastuzumab) arm. In HERA (one-year trastuzumab treatment), the number of patients who discontinued trastuzumab due to cardiac toxicity at 12.6 months median duration of follow-up was 2.6% (44/1678). In BCIRG006, a total of 2.9% (31/1056) of patients in the TCH (docetaxel, carboplatin, trastuzumab) arm (1.5% during the chemotherapy phase and 1.4% during the monotherapy phase) and 5.7% (61/1068) of patients in the AC-TH arm (1.5% during the chemotherapy phase and 4.2% during the monotherapy phase) discontinued trastuzumab due to cardiac toxicity.

Among 64 patients receiving adjuvant chemotherapy (NSABP B31 and NCCTG N9831) who developed congestive heart failure, one patient died of cardiomyopathy, one patient died suddenly without documented etiology and 33 patients were receiving cardiac medication at last follow-up. Approximately 24% of the surviving patients had recovery to a normal LVEF (defined as ≥ 50%) and no symptoms on continuing medical management at the time of last follow-up. Incidence of congestive heart failure (CHF) is presented in Table 1. The safety of continuation or resumption of trastuzumab products in patients with trastuzumab product-induced left ventricular cardiac dysfunction has not been studied.

Table 1: Incidence of Congestive Heart Failure in Adjuvant Breast Cancer Studies
 |  | Incidence of Congestive Heart Failure % (n)
Study | Regimen | Trastuzumab | Control
NSABP B31 & NCCTG N9831 [Median follow-up duration for NSABP B31 and NCCTG N9831 combined was 8.3 years in the AC→paclitaxel + trastuzumab arm.] | AC [Anthracycline (doxorubicin) and cyclophosphamide.] →Paclitaxel+Trastuzumab | 3.2% (64/2000) [Includes 1 patient with fatal cardiomyopathy and 1 patient with sudden death without documented etiology.] | 1.3% (21/1655)
HERA [Includes NYHA II-IV and cardiac death at 12.6 months median duration of follow-up in the one-year trastuzumab arm.] | Chemotherapy→Trastuzumab | 2% (30/1678) | 0.3% (5/1708)
BCIRG006 | AC→Docetaxel+Trastuzumab | 2% (20/1068) | 0.3% (3/1050)
BCIRG006 | Docetaxel+Carboplatin+Trastuzumab | 0.4% (4/1056) | 0.3% (3/1050)

In HERA (one-year trastuzumab treatment), at a median follow-up duration of 8 years, the incidence of severe CHF (NYHA III & IV) was 0.8%, and the rate of mild symptomatic and asymptomatic left ventricular dysfunction was 4.6%.

Table 2: Incidence of Cardiac Dysfunction [Congestive heart failure or significant asymptomatic decrease in LVEF.] in Metastatic Breast Cancer Studies
 |  | Incidence
 |  | NYHA I-IV |  | NYHA III-IV
Study | Event | Trastuzumab | Control | Trastuzumab | Control
H0648g (AC) [Anthracycline (doxorubicin or epirubicin) and cyclophosphamide] | Cardiac Dysfunction | 28% | 7% | 19% | 3%
H0648g (paclitaxel) | Cardiac Dysfunction | 11% | 1% | 4% | 1%
H0649g | Cardiac Dysfunction [Includes 1 patient with fatal cardiomyopathy.] | 7% | N/A | 5% | N/A

In BCIRG006, the incidence of NCI-CTC Grade 3/4 cardiac ischemia/infarction was higher in the trastuzumab containing regimens (AC-TH: 0.3% (3/1068) and TCH: 0.2% (2/1056)) as compared to none in AC-T.

5.2 Infusion Reactions

Infusion reactions consist of a symptom complex characterized by fever and chills, and on occasion included nausea, vomiting, pain (in some cases at tumor sites), headache, dizziness, dyspnea, hypotension, rash, and asthenia [see Adverse Reactions (6.1)].

In post-marketing reports, serious and fatal infusion reactions have been reported. Severe reactions, which include bronchospasm, anaphylaxis, angioedema, hypoxia, and severe hypotension, were usually reported during or immediately following the initial infusion. However, the onset and clinical course were variable, including progressive worsening, initial improvement followed by clinical deterioration, or delayed post-infusion events with rapid clinical deterioration. For fatal events, death occurred within hours to days following a serious infusion reaction.

Interrupt HERZUMA infusion in all patients experiencing dyspnea, clinically significant hypotension, and intervention of medical therapy administered (which may include epinephrine, corticosteroids, diphenhydramine, bronchodilators, and oxygen). Patients should be evaluated and carefully monitored until complete resolution of signs and symptoms. Permanent discontinuation should be strongly considered in all patients with severe infusion reactions.

There are no data regarding the most appropriate method of identification of patients who may safely be retreated with trastuzumab products after experiencing a severe infusion reaction. Prior to resumption of trastuzumab infusion, the majority of patients who experienced a severe infusion reaction were pre-medicated with antihistamines and/or corticosteroids. While some patients tolerated trastuzumab infusions, others had recurrent severe infusion reactions despite pre-medications.

5.3 Embryo-Fetal Toxicity

Trastuzumab products can cause fetal harm when administered to a pregnant woman. In post marketing reports, use of trastuzumab during pregnancy resulted in cases of oligohydramnios and oligohydramnios sequence manifesting as pulmonary hypoplasia, skeletal abnormalities, and neonatal death.

Verify the pregnancy status of females of reproductive potential prior to the initiation of HERZUMA. Advise pregnant women and females of reproductive potential that exposure to HERZUMA during pregnancy or within 7 months prior to conception can result in fetal harm. Advise females of reproductive potential to use effective contraception during treatment and for 7 months following the last dose of HERZUMA [see Use in Specific Populations (8.1, 8.3) and Clinical Pharmacology (12.3)].

5.4 Pulmonary Toxicity

Trastuzumab product use can result in serious and fatal pulmonary toxicity. Pulmonary toxicity includes dyspnea, interstitial pneumonitis, pulmonary infiltrates, pleural effusions, non-cardiogenic pulmonary edema, pulmonary insufficiency and hypoxia, acute respiratory distress syndrome, and pulmonary fibrosis. Such events can occur as sequelae of infusion reactions [see Warnings and Precautions (5.2)]. Patients with symptomatic intrinsic lung disease or with extensive tumor involvement of the lungs, resulting in dyspnea at rest, appear to have more severe toxicity.

5.5 Exacerbation of Chemotherapy-Induced Neutropenia

In randomized, controlled clinical trials, the per-patient incidences of NCI-CTC Grade 3 to 4 neutropenia and of febrile neutropenia were higher in patients receiving trastuzumab in combination with myelosuppressive chemotherapy as compared to those who received chemotherapy alone. The incidence of septic death was similar among patients who received trastuzumab and those who did not [see Adverse Reactions (6.1)].

6 ADVERSE REACTIONS

The following adverse reactions are discussed in greater detail in other sections of the label:

- Cardiomyopathy [see Warnings and Precautions (5.1)]
- Infusion Reactions [see Warnings and Precautions (5.2)]
- Embryo-Fetal Toxicity [see Warnings and Precautions (5.3)]
- Pulmonary Toxicity [see Warnings and Precautions (5.4)]
- Exacerbation of Chemotherapy-induced Neutropenia [see Warnings and Precautions (5.5)]

6.1 Clinical Trials Experience

Because clinical trials are conducted under widely varying conditions, adverse reaction rates observed in the clinical trials of a drug cannot be directly compared to rates in the clinical trials of another drug and may not reflect the rates observed in practice.

The most common adverse reactions in patients receiving trastuzumab products in the adjuvant and metastatic breast cancer setting are fever, nausea, vomiting, infusion reactions, diarrhea, infections, increased cough, headache, fatigue, dyspnea, rash, neutropenia, anemia, and myalgia. Adverse reactions requiring interruption or discontinuation of trastuzumab product treatment include CHF, significant decline in left ventricular cardiac function, severe infusion reactions, and pulmonary toxicity [see Dosage and Administration (2.5)].

In the metastatic gastric cancer setting, the most common adverse reactions (≥ 10%) that were increased (≥ 5% difference) in the trastuzumab arm as compared to the chemotherapy alone arm were neutropenia, diarrhea, fatigue, anemia, stomatitis, weight loss, upper respiratory tract infections, fever, thrombocytopenia, mucosal inflammation, nasopharyngitis, and dysgeusia.

The most common adverse reactions which resulted in discontinuation of treatment on the trastuzumab-containing arm in the absence of disease progression were infection, diarrhea, and febrile neutropenia.

Adjuvant Breast Cancer

The information below reflects exposure to one-year trastuzumab therapy across three randomized, open-label studies, NSABP B31, NCCTG N9831, and HERA with (n = 3678) or without (n = 3363) trastuzumab in the adjuvant treatment of breast cancer.

HERA

Table 3 reflects exposure to trastuzumab in 1678 patients in HERA; the median treatment duration was 51 weeks and median number of infusions was 18 [see Clinical Studies (14.1)].

Table 3: Adverse Reactions (> 1%) in HERA (All Grades) [The incidence of Grade 3 or higher adverse reactions was < 1% in both arms for each listed term.]
Adverse Reactions | Trastuzumab (n = 1678) % | Observation (n = 1708) %
Nervous System
Headache | 10 | 3
Paresthesia | 2 | 0.6
Musculoskeletal
Arthralgia | 8 | 6
Back Pain | 5 | 3
Myalgia | 4 | 1
Bone Pain | 3 | 2
Muscle Spasm | 3 | 0.2
Infections
Nasopharyngitis | 8 | 3
Urinary tract infection | 3 | 0.8
Gastrointestinal
Diarrhea | 7 | 1
Nausea | 6 | 1
Vomiting | 3.5 | 0.6
Constipation | 2 | 1
Dyspepsia | 2 | 0.5
Upper abdominal pain | 2 | 1
General
Pyrexia | 6 | 0.4
Peripheral edema | 5 | 2
Chills | 5 | 0
Asthenia | 4.5 | 2
Influenza-like illness | 2 | 0.2
Respiratory Thoracic Mediastinal
Cough | 5 | 2
Influenza | 4 | 0.5
Dyspnea | 3 | 2
URI | 3 | 1
Rhinitis | 2 | 0.4
Pharyngolaryngeal Pain | 2 | 0.5
Sinusitis | 2 | 0.3
Epistaxis | 2 | 0.06
Cardiac
Hypertension | 4 | 2
Dizziness | 4 | 2
Ejection fraction decreased | 3.5 | 0.6
Palpitations | 3 | 0.7
Cardiac arrhythmias [Higher level grouping term.] | 3 | 1
Cardiac failure (congestive) | 2 | 0.3
Skin & Subcutaneous Tissue
Rash | 4 | 0.6
Nail Disorders | 2 | 0
Pruritus | 2 | 0.6

Clinically relevant adverse reactions in < 1% of patients who received trastuzumab in HERA included hypersensitivity (0.6%), cardiac failure (0.5%), cardiac disorder (0.3%), interstitial pneumonitis (0.2%), pulmonary hypertension (0.2%), ventricular disorder (0.2%), autoimmune thyroiditis (0.3%), and sudden death (0.06%).

Adjuvant Treatment of Breast Cancer with Trastuzumab Beyond One Year

Extending adjuvant treatment beyond one year is not recommended [see Dosage and Administration (2.3)]. In HERA, a comparison of trastuzumab administered once every 3 weeks for two years versus one year was performed. The rate of asymptomatic cardiac dysfunction was increased in the 2-year trastuzumab compared to the 1-year trastuzumab treatment arm (8.1% versus 4.6%, respectively). More patients experienced at least one adverse reaction of Grade 3 or higher in the 2-year trastuzumab treatment arm (20.4%) compared with the one-year trastuzumab treatment arm (16.3%).

NSABP B31 and NCCTG N9831

The safety data from NSABP B31 and NCCTG N9831 were obtained from 3655 patients, of whom 2000 received trastuzumab; the median treatment duration was 51 weeks [see Clinical Studies (14.1)].

In NSABP B31, only Grade 3 to 5 adverse events, treatment-related Grade 2 events, and Grade 2 to 5 dyspnea were collected during and for up to 3 months following protocol-specified treatment. The following non-cardiac adverse reactions of Grade 2 to 5 occurred at an incidence of at least 2% greater among patients receiving trastuzumab plus chemotherapy as compared to chemotherapy alone: fatigue (29.5% vs. 22.4%), infection (24.0% vs. 12.8%), hot flashes (17.1% vs. 15%), anemia (12.3% vs. 6.7%), dyspnea (11.8% vs. 4.6%), rash/desquamation (10.9% vs. 7.6%), leukopenia (10.5% vs. 8.4%), neutropenia (6.4% vs. 4.3%), headache (6.2% vs. 3.8%), pain (5.5% vs. 3%), edema (4.7% vs. 2.7%), and insomnia (4.3% vs. 1.5%). The majority of these events were Grade 2 in severity.

In NCCTG N9831, data collection was limited to the following investigator-attributed treatment-related adverse reactions: NCI-CTC Grade 4 and 5 hematologic toxicities, Grade 3 to 5 non-hematologic toxicities, selected Grade 2 to 5 toxicities associated with taxanes (myalgia, arthralgias, nail changes, motor neuropathy, and sensory neuropathy) and Grade 1 to 5 cardiac toxicities occurring during chemotherapy and/or trastuzumab treatment. The following non-cardiac adverse reactions of Grade 2 to 5 occurred at an incidence of at least 2% greater among patients receiving trastuzumab plus chemotherapy as compared to chemotherapy alone: arthralgia (12.2% vs. 9.1%), nail changes (11.5% vs. 6.8%), dyspnea (2.4% vs. 0.2%), and diarrhea (2.2% vs. 0%). The majority of these events were Grade 2 in severity.

BCIRG006

Safety data from BCIRG006 reflect exposure to trastuzumab as part of an adjuvant treatment regimen from 2124 patients receiving at least one dose of study treatment [AC-TH: n = 1068; TCH: n = 1056]. The overall median treatment duration was 54 weeks in both the AC-TH and TCH arms.

The median number of infusions was 26 in the AC-TH arm and 30 in the TCH arm, including weekly infusions during the chemotherapy phase and once every three week dosing in the monotherapy period [see Clinical Studies (14.1)]. In BCIRG006, the toxicity profile was similar to that reported in NSABP B31, NCCTG N9831, and HERA with the exception of a lower incidence of CHF in the TCH arm.

Metastatic Breast Cancer Studies

The safety of trastuzumab was evaluated in one randomized, open-label study (H0648g) of chemotherapy with (n = 235) or without (n = 234) intravenous trastuzumab in patients with metastatic breast cancer and in one single-arm study (H0649g) in patients with metastatic breast cancer (n = 222) [see Clinical Studies (14.1)]. Patients received 4 mg/kg initial dose of trastuzumab followed by 2 mg/kg weekly. In H0648g, 58% of patients received trastuzumab for ≥ 6 months and 9% received trastuzumab for ≥ 12 months, respectively. In H0649g, 31% of patients received trastuzumab for ≥ 6 months and 16% received trastuzumab for ≥ 12 months, respectively.

Table 4 shows the adverse reactions (≥ 5%) in patients from H0648g and H0649g.

Table 4: Adverse Reactions [Data for trastuzumab single agent were from 4 studies, including 213 patients from H0649g] (≥ 5%) in the Trastuzumab Arms in H0648g and H0649g
 | Trastuzumab n = 352 % | Trastuzumab + Paclitaxel n = 91 % | Paclitaxel n = 95 % | Trastuzumab + AC [Anthracycline (doxorubicin or epirubicin) and cyclophosphamide.] n = 143 % | AC n = 135 %
General
Pain | 47 | 61 | 62 | 57 | 42
Asthenia | 42 | 62 | 57 | 54 | 55
Fever | 36 | 49 | 23 | 56 | 34
Chills | 32 | 41 | 4 | 35 | 11
Headache | 26 | 36 | 28 | 44 | 31
Abdominal pain | 22 | 34 | 22 | 23 | 18
Back pain | 22 | 34 | 30 | 27 | 15
Infection | 20 | 47 | 27 | 47 | 31
Flu syndrome | 10 | 12 | 5 | 12 | 6
Accidental injury | 6 | 13 | 3 | 9 | 4
Allergic reaction | 3 | 8 | 2 | 4 | 2
Gastrointestinal
Nausea | 33 | 51 | 9 | 76 | 77
Diarrhea | 25 | 45 | 29 | 45 | 26
Vomiting | 23 | 37 | 28 | 53 | 49
Anorexia | 14 | 24 | 16 | 31 | 26
Nausea and vomiting | 8 | 14 | 11 | 18 | 9
Respiratory
Cough increased | 26 | 41 | 22 | 43 | 29
Dyspnea | 22 | 27 | 26 | 42 | 25
Rhinitis | 14 | 22 | 5 | 22 | 16
Pharyngitis | 12 | 22 | 14 | 30 | 18
Sinusitis | 9 | 21 | 7 | 13 | 6
Skin
Rash | 18 | 38 | 18 | 27 | 17
Herpes simplex | 2 | 12 | 3 | 7 | 9
Acne | 2 | 11 | 3 | 3 | < 1
Nervous
Insomnia | 14 | 25 | 13 | 29 | 15
Dizziness | 13 | 22 | 24 | 24 | 18
Paresthesia | 9 | 48 | 39 | 17 | 11
Depression | 6 | 12 | 13 | 20 | 12
Peripheral neuritis | 2 | 23 | 16 | 2 | 2
Neuropathy | 1 | 13 | 5 | 4 | 4
Metabolic
Peripheral edema | 10 | 22 | 20 | 20 | 17
Edema | 8 | 10 | 8 | 11 | 5
Cardiovascular
Congestive heart failure | 7 | 11 | 1 | 28 | 7
Tachycardia | 5 | 12 | 4 | 10 | 5
Musculoskeletal
Bone pain | 7 | 24 | 18 | 7 | 7
Arthralgia | 6 | 37 | 21 | 8 | 9
Urogenital
Urinary tract infection | 5 | 18 | 14 | 13 | 7
Blood and Lymphatic
Anemia | 4 | 14 | 9 | 36 | 26
Leukopenia | 3 | 24 | 17 | 52 | 34

Metastatic Gastric Cancer

The safety of trastuzumab was evaluated in patients with previously untreated for metastatic gastric or gastroesophageal junction adenocarcinoma in an open label, multi-center trial (ToGA) [see Clinical Studies (14.3)]. Patients were randomized (1:1) to receive trastuzumab in combination with cisplatin and a fluoropyrimidine (FC+H) (n=294) or chemotherapy alone (FC) (n=290). Patients in the trastuzumab plus chemotherapy arm received trastuzumab 8 mg/kg administered on Day 1 (prior to chemotherapy) followed by 6 mg/kg every 21 days until disease progression. Cisplatin was administered at 80 mg/m^2 on Day 1 and the fluoropyrimidine was administered as either capecitabine 1000 mg/m^2 orally twice a day on Days 1 to 14 or 5-fluorouracil 800 mg/m^2/day as a continuous intravenous infusion Days 1 through 5. Chemotherapy was administered for six 21 day cycles. Median duration of trastuzumab treatment was 21 weeks and the median number of trastuzumab infusions administered was eight.

Table 5: Adverse Reactions (All Grades ≥ 5% or Grade 3-4 ≥ 1% between Arms) in ToGA
Adverse Reactions | Trastuzumab + FC (N = 294) % |  | FC (N = 290) %
Adverse Reactions | All Grades | Grades 3-4 | All Grades | Grades 3-4
Investigations
Neutropenia | 78 | 34 | 73 | 29
Hypokalemia | 28 | 10 | 24 | 6
Anemia | 28 | 12 | 21 | 10
Thrombocytopenia | 16 | 5 | 11 | 3
Blood and Lymphatic System Disorders
Febrile Neutropenia | — | 5 | — | 3
Gastrointestinal Disorders
Diarrhea | 37 | 9 | 28 | 4
Stomatitis | 24 | 1 | 15 | 2
Dysphagia | 6 | 2 | 3 | < 1
General
Fatigue | 35 | 4 | 28 | 2
Fever | 18 | 1 | 12 | 0
Mucosal Inflammation | 13 | 2 | 6 | 1
Chills | 8 | < 1 | 0 | 0
Metabolism and Nutrition Disorders
Weight Decrease | 23 | 2 | 14 | 2
Infections and Infestations
Upper Respiratory Tract Infections | 19 | 0 | 10 | 0
Nasopharyngitis | 13 | 0 | 6 | 0
Renal and Urinary Disorders
Renal Failure and Impairment | 18 | 3 | 15 | 2
Nervous System Disorders
Dysgeusia | 10 | 0 | 5 | 0

The following subsections provide additional detail regarding adverse reactions observed in clinical trials of adjuvant breast cancer, metastatic breast cancer, metastatic gastric cancer, or post-marketing experience.

Cardiomyopathy

Serial measurement of cardiac function (LVEF) was obtained in clinical trials in the adjuvant treatment of breast cancer. In HERA, the median duration of follow-up was 12.6 months (12.4 months in the observation arm; 12.6 months in the 1-year trastuzumab arm); and in NSABP B31 and NCCTG N9831, 7.9 years in the AC-T arm, 8.3 years in the AC-TH arm. Following initiation of trastuzumab therapy, the incidence of new-onset dose-limiting myocardial dysfunction was higher among patients receiving trastuzumab and paclitaxel as compared to those receiving paclitaxel alone in NSABP B31 and NCCTG N9831, and in patients receiving one-year trastuzumab monotherapy compared to observation in HERA (see Table 6, Figures 1 and 2). The incidence of new-onset cardiac dysfunction, as measured by LVEF, remained similar when compared to the analysis performed at a median follow-up of 2.0 years in the AC-TH arm. This analysis showed evidence of reversibility of left ventricular dysfunction, with 64.5% of patients who experienced symptomatic CHF in the AC-TH group being asymptomatic at latest follow-up, and 90.3% having full or partial LVEF recovery.

Table 6: Myocardial Dysfunction (by LVEF) in NSABP B31, NCCTG N9831, HERA and BCIRG006 [For NSABP B31, NCCTG N9831 and HERA, events are counted from the beginning of trastuzumab treatment. For BCIRG006, events are counted from the date of randomization.]
Study and Arm | LVEF < 50% and Decrease from Baseline |  |  | LVEF Decrease
Study and Arm | LVEF < 50% | ≥ 10% decrease | ≥ 16% decrease | < 20% and ≥ 10% | ≥ 20%
NSABP B31 & NCCTG N9831 [NSABP B31 and NCCTG N9831 regimens: doxorubicin and cyclophosphamide followed by paclitaxel (AC→T) or paclitaxel plus trastuzumab (AC→TH).] [Median duration of follow-up for NSABP B31 and NCCTG N9831 combined was 8.3 years in the AC→TH arm.]
AC→TH (n = 1856) | 23.1% (428) | 18.5% (344) | 11.2% (208) | 37.9% (703) | 8.9% (166)
AC→T (n = 1170) | 11.7% (137) | 7.0% (82) | 3.0% (35) | 22.1% (259) | 3.4% (40)
HERA [Median follow-up duration of 12.6 months in the one-year trastuzumab treatment arm.]
Trastuzumab (n = 1678) | 8.6% (144) | 7.0% (118) | 3.8% (64) | 22.4% (376) | 3.5% (59)
Observation (n = 1708) | 2.7% (46) | 2.0% (35) | 1.2% (20) | 11.9% (204) | 1.2% (21)
BCIRG006 [BCIRG006 regimens: doxorubicin and cyclophosphamide followed by docetaxel (AC→T) or docetaxel plus trastuzumab (AC→TH); docetaxel and carboplatin plus trastuzumab (TCH).]
TCH (n = 1056) | 8.5% (90) | 5.9% (62) | 3.3% (35) | 34.5% (364) | 6.3% (67)
AC→TH (n = 1068) | 17% (182) | 13.3% (142) | 9.8% (105) | 44.3% (473) | 13.2% (141)
AC→T (n = 1050) | 9.5% (100) | 6.6% (69) | 3.3% (35) | 34% (357) | 5.5% (58)

Figure 1: NSABP B31 and NCCTG N9831: Cumulative Incidence of Time to First LVEF Decline of ≥ 10 Percentage Points from Baseline and to Below 50% with Death as a Competing Risk Event

Time 0 is initiation of paclitaxel or trastuzumab + paclitaxel therapy.

Figure 2: HERA: Cumulative Incidence of Time to First LVEF Decline of ≥ 10 Percentage Points from Baseline and to Below 50% with Death as a Competing Risk Event

Time 0 is the date of randomization.

Figure 3: BCIRG006: Cumulative Incidence of Time to First LVEF Decline of ≥ 10 Percentage Points from Baseline and to Below 50% with Death as a Competing Risk Event

Time 0 is the date of randomization.

The incidence of congestive heart failure among patients in the metastatic breast cancer trials was classified for severity using the New York Heart Association classification system (I to IV, where IV is the most severe level of cardiac failure) (see Table 2). In the metastatic breast cancer trials, the probability of cardiac dysfunction was highest in patients who received trastuzumab concurrently with anthracyclines.

In ToGA, 5% of patients in the trastuzumab plus chemotherapy arm compared to 1.1% of patients in the chemotherapy alone arm had LVEF value below 50% with a ≥ 10% absolute decrease in LVEF from pretreatment values.

Infusion Reactions

During the first infusion with trastuzumab, the symptoms most commonly reported were chills and fever, occurring in approximately 40% of patients in clinical trials. Symptoms were treated with acetaminophen, diphenhydramine, and meperidine (with or without reduction in the rate of trastuzumab infusion); permanent discontinuation of trastuzumab for infusion reactions was required in < 1% of patients. Other signs and/or symptoms may include nausea, vomiting, pain (in some cases at tumor sites), rigors, headache, dizziness, dyspnea, hypotension, elevated blood pressure, rash, and asthenia. Infusion reactions occurred in 21% and 35% of patients, and were severe in 1.4% and 9% of patients, on second or subsequent trastuzumab infusions administered as monotherapy or in combination with chemotherapy, respectively. In the post-marketing setting, severe infusion reactions, including hypersensitivity, anaphylaxis, and angioedema have been reported.

Anemia

In randomized controlled clinical trials, the overall incidence of anemia (30% vs. 21% [H0648g]), of selected NCI-CTC Grade 2–5 anemia (12.3% vs. 6.7% [NSABP B31]), and of anemia requiring transfusions (0.1% vs. 0 patients [NCCTG N9831]) were increased in patients receiving trastuzumab and chemotherapy compared with those receiving chemotherapy alone. Following the administration of trastuzumab as a single agent (H0649g), the incidence of NCI-CTC Grade 3 anemia was < 1%. In ToGA (metastatic gastric cancer), on the trastuzumab containing arm as compared to the chemotherapy alone arm, the overall incidence of anemia was 28% compared to 21% and of NCI-CTC Grade 3/4 anemia was 12.2% compared to 10.3%.

Neutropenia

In randomized controlled clinical trials in the adjuvant setting, the incidence of selected NCI-CTC Grade 4 to 5 neutropenia (1.7% vs. 0.8% [NCCTG N9831]) and of selected Grade 2 to 5 neutropenia (6.4% vs. 4.3% [NSABP B31]) were increased in patients receiving trastuzumab and chemotherapy compared with those receiving chemotherapy alone. In a randomized, controlled trial in patients with metastatic breast cancer, the incidences of NCI-CTC Grade 3/4 neutropenia (32% vs. 22%) and of febrile neutropenia (23% vs. 17%) were also increased in patients randomized to trastuzumab in combination with myelosuppressive chemotherapy as compared to chemotherapy alone. In ToGA (metastatic gastric cancer) on the trastuzumab containing arm as compared to the chemotherapy alone arm, the incidence of NCI-CTC Grade 3/4 neutropenia was 36.8% compared to 28.9%; febrile neutropenia 5.1% compared to 2.8%.

Infection

The overall incidences of infection (46% vs. 30% [H0648g]), of selected NCI-CTC Grade 2 to 5 infection/febrile neutropenia (24.3% vs. 13.4% [NSABP B31]) and of selected Grade 3 to 5 infection/febrile neutropenia (2.9% vs. 1.4% [NCCTG N9831]) were higher in patients receiving trastuzumab and chemotherapy compared with those receiving chemotherapy alone. The most common site of infections in the adjuvant setting involved the upper respiratory tract, skin, and urinary tract.

In BCIRG006, the overall incidence of infection was higher with the addition of trastuzumab to AC-T but not to TCH [44% (AC-TH), 37% (TCH), 38% (AC-T)]. The incidences of NCI-CTC Grade 3 to 4 infection were similar [25% (AC-TH), 21% (TCH), 23% (AC-T)] across the three arms.

In a randomized, controlled trial in treatment of metastatic breast cancer, the reported incidence of febrile neutropenia was higher (23% vs. 17%) in patients receiving trastuzumab in combination with myelosuppressive chemotherapy as compared to chemotherapy alone.

Pulmonary Toxicity

Adjuvant Breast Cancer

Among women receiving adjuvant therapy for breast cancer, the incidence of selected NCI-CTC Grade 2 to 5 pulmonary toxicity (14.3% vs. 5.4% [NSABP B31]) and of selected NCI-CTC Grade 3 to 5 pulmonary toxicity and spontaneous reported Grade 2 dyspnea (3.4% vs. 0.9% [NCCTG N9831]) was higher in patients receiving trastuzumab and chemotherapy compared with chemotherapy alone. The most common pulmonary toxicity was dyspnea (NCI-CTC Grade 2 to 5: 11.8% vs. 4.6% [NSABP B31]; NCI-CTC Grade 2 to 5: 2.4% vs. 0.2% [NCCTG N9831]).

Pneumonitis/pulmonary infiltrates occurred in 0.7% of patients receiving trastuzumab compared with 0.3% of those receiving chemotherapy alone. Fatal respiratory failure occurred in 3 patients receiving trastuzumab, one as a component of multi-organ system failure, as compared to 1 patient receiving chemotherapy alone.

In HERA, there were 4 cases of interstitial pneumonitis in the one-year trastuzumab treatment arm compared to none in the observation arm at a median follow-up duration of 12.6 months.

Metastatic Breast Cancer

Among women receiving trastuzumab for treatment of metastatic breast cancer, the incidence of pulmonary toxicity was also increased. Pulmonary adverse events have been reported in the post-marketing experience as part of the symptom complex of infusion reactions. Pulmonary events include bronchospasm, hypoxia, dyspnea, pulmonary infiltrates, pleural effusions, non-cardiogenic pulmonary edema, and acute respiratory distress syndrome. For a detailed description, see Warnings and Precautions (5.4).

Thrombosis/Embolism

In 4 randomized, controlled clinical trials, the incidence of thrombotic adverse events was higher in patients receiving trastuzumab and chemotherapy compared to chemotherapy alone in three studies (2.6% vs. 1.5% [NSABP B31], 2.5% and 3.7% vs. 2.2% [BCIRG006] and 2.1% vs. 0% [H0648g]).

Diarrhea

Among women receiving adjuvant therapy for breast cancer, the incidence of NCI-CTC Grade 2–5 diarrhea (6.7% vs. 5.4% [NSABP B31]) and of NCI-CTC Grade 3 to 5 diarrhea (2.2% vs. 0% [NCCTG N9831]), and of Grade 1 to 4 diarrhea (7% vs. 1% [HERA; one-year trastuzumab treatment at 12.6 months median duration of follow-up]) were higher in patients receiving trastuzumab as compared to controls. In BCIRG006, the incidence of Grade 3 to 4 diarrhea was higher [5.7% AC-TH, 5.5% TCH vs. 3.0% AC-T] and of Grade 1 to 4 was higher [51% AC-TH, 63% TCH vs. 43% AC-T] among women receiving trastuzumab. Of patients receiving trastuzumab as a single agent for the treatment of metastatic breast cancer, 25% experienced diarrhea. An increased incidence of diarrhea was observed in patients receiving trastuzumab in combination with chemotherapy for treatment of metastatic breast cancer.

Renal Toxicity

In ToGA (metastatic gastric cancer) on the trastuzumab-containing arm as compared to the chemotherapy alone arm the incidence of renal impairment was 18% compared to 14.5%. Severe (Grade 3/4) renal failure was 2.7% on the trastuzumab-containing arm compared to 1.7% on the chemotherapy only arm. Treatment discontinuation for renal insufficiency/failure was 2% on the trastuzumab-containing arm and 0.3% on the chemotherapy only arm.

In the post-marketing setting, rare cases of nephrotic syndrome with pathologic evidence of glomerulopathy have been reported. The time to onset ranged from 4 months to approximately 18 months from initiation of trastuzumab therapy. Pathologic findings included membranous glomerulonephritis, focal glomerulosclerosis, and fibrillary glomerulonephritis. Complications included volume overload and congestive heart failure.

6.2 Post-Marketing Experience

The following adverse reactions have been identified during post-approval use of trastuzumab products. Because these reactions are reported voluntarily from a population of uncertain size, it is not always possible to reliably estimate their frequency or establish a causal relationship to drug exposure.

- Infusion reaction [see Warnings and Precautions (5.2)]
- Oligohydramnios or oligohydramnios sequence, including pulmonary hypoplasia, skeletal abnormalities, and neonatal death [see Warnings and Precautions (5.3)]
- Glomerulopathy [see Adverse Reactions (6.1)]
- Immune thrombocytopenia
- Tumor lysis syndrome (TLS): Cases of possible TLS have been reported in patients treated with trastuzumab products. Patients with significant tumor burden (e.g. bulky metastases) may be at a higher risk. Patients could present with hyperuricemia, hyperphosphatemia, and acute renal failure which may represent possible TLS. Providers should consider additional monitoring and/or treatment as clinically indicated.

7 DRUG INTERACTIONS

Anthracyclines

Patients who receive anthracycline after stopping trastuzumab products may be at increased risk of cardiac dysfunction because of trastuzumab products' estimated long washout period [see Clinical Pharmacology (12.3)]. If possible, avoid anthracycline-based therapy for up to 7 months after stopping trastuzumab products. If anthracyclines are used, closely monitor the patient's cardiac function.

8 USE IN SPECIFIC POPULATIONS

8.1 Pregnancy

Risk Summary

Trastuzumab products can cause fetal harm when administered to a pregnant woman. In post-marketing reports and published literature, use of trastuzumab products during pregnancy resulted in cases of oligohydramnios and of oligohydramnios sequence, manifesting as pulmonary hypoplasia, skeletal abnormalities, and neonatal death [see Data]. Apprise the patient of the potential risks to a fetus. There are clinical considerations if a trastuzumab product is used in a pregnant woman or if a patient becomes pregnant within 7 months following the last dose of a trastuzumab product [see Clinical Considerations].

The background risk of major birth defects and miscarriage for the indicated population is unknown. In the U.S. general population, the estimated background risk of major birth defects and miscarriage in clinically recognized pregnancies is 2% to 4% and 15% to 20%, respectively.

Clinical Considerations

Fetal/Neonatal Adverse Reactions

Monitor women who received HERZUMA during pregnancy or within 7 months prior to conception for oligohydramnios. If oligohydramnios occurs, perform fetal/neonatal testing that is appropriate for gestational age and consistent with community standards of care.

Data

Human Data

In post-marketing reports and published literature, use of trastuzumab products during pregnancy resulted in cases of oligohydramnios and of oligohydramnios sequence. Fetal manifestations included pulmonary hypoplasia, skeletal abnormalities, and neonatal death. These case reports described oligohydramnios in pregnant women who received trastuzumab either alone or in combination with chemotherapy. In most reported cases, amniotic fluid index increased after trastuzumab was stopped. In reported cases where trastuzumab therapy was resumed after amniotic index improved, oligohydramnios recurred.

Animal Data

In studies where trastuzumab was administered to pregnant Cynomolgus monkeys during the period of organogenesis at doses up to 25 mg/kg given twice weekly (up to 25 times the recommended weekly human dose of 2 mg/kg), trastuzumab crossed the placental barrier during the early (Gestation Days 20 to 50) and late (Gestation Days 120 to 150) phases of gestation. The resulting concentrations of trastuzumab in fetal serum and amniotic fluid were approximately 33% and 25%, respectively, of those present in the maternal serum but were not associated with adverse developmental effects.

8.2 Lactation

Risk Summary

There is no information regarding the presence of trastuzumab products in human milk, the effects on the breastfed infant, or the effects on milk production. Published data suggest human IgG is present in human milk but does not enter the neonatal and infant circulation in substantial amounts. Trastuzumab was present in the milk of lactating Cynomolgus monkeys but not associated with neonatal toxicity [see Data]. Consider the developmental and health benefits of breastfeeding along with the mother's clinical need for HERZUMA treatment and any potential adverse effects on the breastfed child from HERZUMA or from the underlying maternal condition. This consideration should also take into account the trastuzumab product wash out period of 7 months [see Clinical Pharmacology (12.3)].

Data

In lactating Cynomolgus monkeys, trastuzumab was present in breast milk at about 0.3% of maternal serum concentrations after pre- (beginning Gestation Day 120) and post-partum (through Post-partum Day 28) doses of 25 mg/kg administered twice weekly (25 times the recommended weekly human dose of 2 mg/kg of trastuzumab products). Infant monkeys with detectable serum levels of trastuzumab did not exhibit any adverse effects on growth or development from birth to 1 month of age.

8.3 Females and Males of Reproductive Potential

Pregnancy Testing

Verify the pregnancy status of females of reproductive potential prior to the initiation of HERZUMA.

Contraception

Females

Trastuzumab products can cause embryo-fetal harm when administered during pregnancy. Advise females of reproductive potential to use effective contraception during treatment with HERZUMA and for 7 months following the last dose of HERZUMA [see Use in Specific Populations (8.1) and Clinical Pharmacology (12.3)].

8.4 Pediatric Use

The safety and effectiveness of HERZUMA in pediatric patients have not been established.

8.5 Geriatric Use

Trastuzumab has been administered to 386 patients who were 65 years of age or over (253 in the adjuvant treatment and 133 in metastatic breast cancer treatment settings). The risk of cardiac dysfunction was increased in geriatric patients as compared to younger patients in both those receiving treatment for metastatic disease in H0648g and H0649g, or adjuvant therapy in NSABP B31 and NCCTG N9831. Limitations in data collection and differences in study design of the 4 studies of trastuzumab in adjuvant treatment of breast cancer preclude a determination of whether the toxicity profile of trastuzumab in older patients is different from younger patients. The reported clinical experience is not adequate to determine whether the efficacy improvements (ORR, TTP, OS, DFS) of trastuzumab treatment in older patients is different from that observed in patients < 65 years of age for metastatic disease and adjuvant treatment.

In ToGA (metastatic gastric cancer), of the 294 patients treated with trastuzumab, 108 (37%) were 65 years of age or older, while 13 (4.4%) were 75 and over. No overall differences in safety or effectiveness were observed.

11 DESCRIPTION

Trastuzumab-pkrb is a humanized IgG1 kappa monoclonal antibody that selectively binds with high affinity to the extracellular domain of the human epidermal growth factor receptor 2 protein, HER2. Trastuzumab-pkrb is produced by recombinant DNA technology in a mammalian cell (Chinese Hamster Ovary) culture.

HERZUMA (trastuzumab-pkrb) for injection is a sterile, white to pale yellow, preservative-free lyophilized powder with a cake-like appearance, for intravenous administration.

Each multiple-dose vial of HERZUMA delivers 420 mg trastuzumab-pkrb, 839 mg α,α-trehalose dihydrate, 9.5 mg L-histidine HCl, 6.1 mg L-histidine, and 1.7 mg polysorbate 20. Reconstitution with 20 mL of the appropriate diluent (BWFI or SWFI) yields a solution containing 21 mg/mL trastuzumab-pkrb that delivers 20 mL (420 mg trastuzumab-pkrb), at a pH of approximately 6. If HERZUMA is reconstituted with SWFI without preservative, the reconstituted solution is considered single-dose.

Each single-dose vial of HERZUMA delivers 150 mg trastuzumab-pkrb, 299.6 mg α,α-trehalose dihydrate, 3.4 mg L-histidine HCl, 2.2 mg L-histidine, and 0.6 mg polysorbate 20. Reconstitution with 7.4 mL of sterile water for injection (SWFI) yields a solution containing 21 mg/mL trastuzumab-pkrb that delivers 7.15 mL (150 mg trastuzumab-pkrb), at a pH of approximately 6.

12 CLINICAL PHARMACOLOGY

12.1 Mechanism of Action

The HER2 (or c-erbB2) proto-oncogene encodes a transmembrane receptor protein of 185 kDa, which is structurally related to the epidermal growth factor receptor. Trastuzumab products have been shown, in both in vitro assays and in animals, to inhibit the proliferation of human tumor cells that overexpress HER2.

Trastuzumab products are mediators of antibody-dependent cellular cytotoxicity (ADCC). In vitro, trastuzumab product-mediated ADCC has been shown to be preferentially exerted on HER2 overexpressing cancer cells compared with cancer cells that do not overexpress HER2.

12.2 Pharmacodynamics

Trastuzumab product exposure-response relationships and the time course of pharmacodynamic responses are not fully characterized.

Cardiac Electrophysiology

The effects of trastuzumab on electrocardiographic (ECG) endpoints, including QTc interval duration, were evaluated in patients with HER2 positive solid tumors. Trastuzumab had no clinically relevant effect on the QTc interval duration and there was no apparent relationship between serum trastuzumab concentrations and change in QTcF interval duration in patients with HER2 positive solid tumors.

12.3 Pharmacokinetics

The pharmacokinetics of trastuzumab were evaluated in a pooled population pharmacokinetic (PK) model analysis of 1,582 subjects with primarily breast cancer and metastatic gastric cancer (MGC) receiving intravenous trastuzumab. Total trastuzumab clearance increases with decreasing concentrations due to parallel linear and non-linear elimination pathways.

Although the average trastuzumab exposure was higher following the first cycle in breast cancer patients receiving the once every three week schedule compared to the weekly schedule of trastuzumab, the average steady-state exposure was essentially the same at both dosages. The average trastuzumab exposure following the first cycle and at steady state as well as the time to steady state was higher in breast cancer patients compared to MGC patients at the same dosage; however, the reason for this exposure difference is unknown. Additional predicted trastuzumab exposure and PK parameters following the first trastuzumab cycle and at steady state exposure are described in Tables 7 and 8, respectively.

Population PK based simulations indicate that following discontinuation of trastuzumab, concentrations in at least 95% of breast cancer patients and MGC patients will decrease to approximately 3% of the population predicted steady-state trough serum concentration (approximately 97% washout) by 7 months [see Warnings and Precautions (5.1) and Use in Specific Populations (8.1, 8.3)].

Table 7: Population Predicted Cycle 1 PK Exposures (Median with 5th to 95th Percentiles) in Breast Cancer and MGC Patients
Schedule | Primary tumor type | N | Cmin (mcg/mL) | Cmax (mcg/mL) | AUC0-21 days (mcg.day/mL)
8 mg/kg + 6 mg/kg q3w | Breast cancer | 1195 | 29.4 (5.8 to 59.5) | 178 (117 to 291) | 1373 (736 to 2245)
8 mg/kg + 6 mg/kg q3w | MGC | 274 | 23.1 (6.1 to 50.3) | 132 (84.2 to 225) | 1109 (588 to 1938)
4 mg/kg + 2 mg/kg qw | Breast cancer | 1195 | 37.7 (12.3 to 70.9) | 88.3 (58 to 144) | 1066 (586 to 1754)

Table 8: Population Predicted Steady State PK Exposures (Median with 5th to 95th Percentiles) in Breast Cancer and MGC Patients
Schedule | Primary tumor type | N | Cmin,ss [Steady-state trough serum concentration of trastuzumab] (mcg/mL) | Cmax,ss [Maximum steady-state serum concentration of trastuzumab] (mcg/mL) | AUCss, 0-21 days (mcg.day/mL) | Time to steady-state (week) | Total CL range at steady-state (L/day)
8 mg/kg + 6 mg/kg q3w | Breast cancer | 1195 | 47.4 (5 to 115) | 179 (107 to 309) | 1794 (673 to 3618) | 12 | 0.173 to 0.283
8 mg/kg + 6 mg/kg q3w | MGC | 274 | 32.9 (6.1 to 88.9) | 131 (72.5 to 251) | 1338 (557 to 2875) | 9 | 0.189 to 0.337
4 mg/kg + 2 mg/kg qw | Breast cancer | 1195 | 66.1 (14.9 to 142) | 109 (51.0 to 209) | 1765 (647 to 3578) | 12 | 0.201 to 0.244

Specific Populations

Based on a population pharmacokinetic analysis, no clinically significant differences were observed in the pharmacokinetics of trastuzumab based on age (< 65 (n=1294); ≥ 65 (n=288)), race (Asian (n=264); non-Asian (n=1324)) and renal impairment (mild (creatinine clearance [CLcr] 60 to 90 mL/min) (n=636) or moderate (CLcr 30 to 60 mL/min) (n=133)). The pharmacokinetics of trastuzumab products in patients with severe renal impairment, end-stage renal disease with or without hemodialysis, or hepatic impairment is unknown.

Drug Interaction Studies

There have been no formal drug interaction studies performed with trastuzumab products in humans. Clinically significant interactions between trastuzumab and concomitant medications used in clinical trials have not been observed.

Paclitaxel and doxorubicin: Concentrations of paclitaxel and doxorubicin and their major metabolites (i.e., 6-α hydroxyl-paclitaxel [POH], and doxorubicinol [DOL], respectively) were not altered in the presence of trastuzumab when used as combination therapy in clinical trials. Trastuzumab concentrations were not altered as part of this combination therapy.

Docetaxel and carboplatin: When trastuzumab was administered in combination with docetaxel or carboplatin, neither the plasma concentrations of docetaxel or carboplatin nor the plasma concentrations of trastuzumab were altered.

Cisplatin and capecitabine: In a drug interaction substudy conducted in patients in ToGA, the pharmacokinetics of cisplatin, capecitabine and their metabolites were not altered when administered in combination with trastuzumab.

12.6 Immunogenicity

The observed incidence of anti-drug antibodies is highly dependent on the sensitivity and specificity of the assay. Differences in assay methods preclude meaningful comparisons of the incidence of anti-drug antibodies in the studies described below with the incidence of anti-drug antibodies in other studies, including those of trastuzumab or of other trastuzumab products.
Among 903 women with metastatic breast cancer, human anti human antibody (HAHA) to trastuzumab was detected in one patient using an enzyme linked immunosorbent assay (ELISA). This patient did not experience an allergic reaction. Samples for assessment of HAHA were not collected in studies of adjuvant breast cancer.
The clinical relevance of the development of anti-trastuzumab antibodies after treatment with trastuzumab is not known.

13 NONCLINICAL TOXICOLOGY

13.1 Carcinogenesis, Mutagenesis, Impairment of Fertility

Trastuzumab products have not been tested for carcinogenic potential.

No evidence of mutagenic activity was observed when trastuzumab was tested in the standard Ames bacterial and human peripheral blood lymphocyte mutagenicity assays, at concentrations of up to 5000 mcg/mL. In an in vivo micronucleus assay, no evidence of chromosomal damage to mouse bone marrow cells was observed following bolus intravenous doses of up to 118 mg/kg of trastuzumab.

A fertility study was conducted in female Cynomolgus monkeys at doses up to 25 times the weekly recommended human dose of 2 mg/kg of trastuzumab and has revealed no evidence of impaired fertility, as measured by menstrual cycle duration and female sex hormone levels.

14 CLINICAL STUDIES

14.1 Adjuvant Breast Cancer

The safety and efficacy of trastuzumab in women receiving adjuvant chemotherapy for HER2 overexpressing breast cancer were evaluated in an integrated analysis of two randomized, open-label, clinical trials (NSABP B31 and NCCTG N9831) with a total of 4063 women at the protocol-specified final overall survival analysis, a third randomized, open-label, clinical trial (HERA) with a total of 3386 women at definitive Disease-Free Survival analysis for one-year trastuzumab treatment versus observation, and a fourth randomized, open-label clinical trial with a total of 3222 patients (BCIRG006).

NSABP B31 and NCCTG N9831

In NSABP B31 and NCCTG N9831, breast tumor specimens were required to show HER2 overexpression (3+ by IHC) or gene amplification (by FISH). HER2 testing was verified by a central laboratory prior to randomization (NCCTG N9831) or was required to be performed at a reference laboratory (NSABP B31). Patients with a history of active cardiac disease based on symptoms, abnormal electrocardiographic, radiologic, or left ventricular ejection fraction findings or uncontrolled hypertension (diastolic > 100 mm Hg or systolic > 200 mm Hg) were not eligible.

Patients were randomized (1:1) to receive doxorubicin and cyclophosphamide followed by paclitaxel (AC→paclitaxel) alone or paclitaxel plus trastuzumab (AC→paclitaxel + trastuzumab). In both trials, patients received four 21-day cycles of doxorubicin 60 mg/m^2 and cyclophosphamide 600 mg/m^2. Paclitaxel was administered either weekly (80 mg/m^2) or every 3 weeks (175 mg/m^2) for a total of 12 weeks in NSABP B31; paclitaxel was administered only by the weekly schedule in NCCTG N9831. Trastuzumab was administered at 4 mg/kg on the day of initiation of paclitaxel and then at a dose of 2 mg/kg weekly for a total of 52 weeks. Trastuzumab treatment was permanently discontinued in patients who developed congestive heart failure, or persistent/recurrent LVEF decline [see Dosage and Administration (2.5)]. Radiation therapy, if administered, was initiated after the completion of chemotherapy. Patients with ER+ and/or PR+ tumors received hormonal therapy. The major efficacy outcome measure of the combined efficacy analysis was Disease-Free Survival (DFS), defined as the time from randomization to recurrence, occurrence of contralateral breast cancer, other second primary cancer, or death. An additional efficacy outcome measure was overall survival (OS).

A total of 3752 patients were included in the joint efficacy analysis of DFS following a median follow-up of 2.0 years in the AC→paclitaxel + trastuzumab arm. The pre-planned final OS analysis from the joint analysis included 4063 patients and was performed when 707 deaths had occurred after a median follow-up of 8.3 years in the AC→paclitaxel + trastuzumab arm. The data from both arms in NSABP B31 and two of the three study arms in NCCTG N9831 were pooled for efficacy analyses.

The patients included in the DFS analysis had a median age of 49 years (range, 22 to 80 years; 6% > 65 years), 84% were White, 7% Black, 4% Hispanic, and 4% Asian/Pacific Islander. Disease characteristics included 90% infiltrating ductal histology, 38% T1, 91% nodal involvement, 27% intermediate and 66% high grade pathology, and 53% ER+ and/or PR+ tumors.

HERA

In HERA, breast tumor specimens were required to show HER2 overexpression (3+ by IHC) or gene amplification (by FISH) as determined at a central laboratory. Patients with node-negative disease were required to have ≥ T1c primary tumor. Patients with a history of congestive heart failure or LVEF < 55%, uncontrolled arrhythmias, angina requiring medication, clinically significant valvular heart disease, evidence of transmural infarction on ECG, poorly controlled hypertension (systolic > 180 mm Hg or diastolic > 100 mm Hg) were not eligible.

Patients were randomized (1:1:1) upon completion of definitive surgery, and at least four cycles of chemotherapy to receive no additional treatment, or one year of trastuzumab treatment or two years of trastuzumab treatment. Patients undergoing a lumpectomy had also completed standard radiotherapy. Patients with ER+ and/or PgR+ disease received systemic adjuvant hormonal therapy at investigator discretion. Trastuzumab was administered with an initial dose of 8 mg/kg followed by subsequent doses of 6 mg/kg once every three weeks. The major efficacy outcome measure was Disease-Free Survival (DFS), defined as in NSABP B31 and NCCTG N9831.

HERA was designed to compare one and two years of once every three week trastuzumab treatment versus observation in patients with HER2 positive EBC following surgery, established chemotherapy and radiotherapy (if applicable). A protocol specified interim efficacy analysis comparing one-year trastuzumab treatment to observation was performed at a median follow-up duration of 12.6 months in the trastuzumab arm.

Among the 3386 patients randomized to the observation (n = 1693) and trastuzumab one year (n = 1693) treatment arms, the median age was 49 years (range 21 to 80), 83% were White, and 13% were Asian. Disease characteristics: 94% infiltrating ductal carcinoma, 50% ER+ and/or PgR+, 57% node positive, 32% node negative, and in 11% of patients, nodal status was not assessable due to prior neo-adjuvant chemotherapy. Ninety-six percent (1055/1098) of patients with node-negative disease had high-risk features: among the 1098 patients with node-negative disease, 49% (543) were ER- and PgR-, and 47% (512) were ER and/or PgR + and had at least one of the following high-risk features: pathological tumor size greater than 2 cm, Grade 2 to 3, or age < 35 years. Prior to randomization, 94% of patients had received anthracycline-based chemotherapy regimens.

After the DFS results comparing observation to one-year trastuzumab treatment were disclosed, a prospectively planned analysis that included comparison of one year versus two years of trastuzumab treatment at a median follow-up duration of 8 years was performed. Based on this analysis, extending trastuzumab treatment for a duration of two years did not show additional benefit over treatment for one year [Hazard Ratios of two-years trastuzumab versus one-year trastuzumab treatment in the intent to treat (ITT) population for Disease-Free Survival (DFS) = 0.99 (95% CI: 0.87, 1.13), p-value = 0.90 and Overall Survival (OS) = 0.98 (0.83, 1.15); p-value = 0.78].

BCIRG006

In BCIRG006, breast tumor specimens were required to show HER2 gene amplification (FISH+ only) as determined at a central laboratory. Patients were required to have either node-positive disease, or node-negative disease with at least one of the following high-risk features: ER/PR-negative, tumor size > 2 cm, age < 35 years, or histologic and/or nuclear Grade 2 or 3. Patients with a history of CHF, myocardial infarction, Grade 3 or 4 cardiac arrhythmia, angina requiring medication, clinically significant valvular heart disease, poorly controlled hypertension (diastolic > 100 mm Hg), any T4 or N2, or known N3 or M1 breast cancer were not eligible.

Patients were randomized (1:1:1) to receive doxorubicin and cyclophosphamide followed by docetaxel (AC-T), doxorubicin and cyclophosphamide followed by docetaxel plus trastuzumab (AC-TH), or docetaxel and carboplatin plus trastuzumab (TCH). In both the AC-T and AC-TH arms, doxorubicin 60 mg/m^2 and cyclophosphamide 600 mg/m^2 were administered every 3 weeks for four cycles; docetaxel 100 mg/m^2 was administered every 3 weeks for four cycles. In the TCH arm, docetaxel 75 mg/m^2 and carboplatin (at a target AUC of 6 mg/mL/min as a 30- to 60-minute infusion) were administered every 3 weeks for six cycles. Trastuzumab was administered weekly (initial dose of 4 mg/kg followed by weekly dose of 2 mg/kg) concurrently with either T or TC, and then every 3 weeks (6 mg/kg) as monotherapy for a total of 52 weeks. Radiation therapy, if administered, was initiated after completion of chemotherapy. Patients with ER+ and/or PR+ tumors received hormonal therapy. Disease-Free Survival (DFS) was the major efficacy outcome measure.

Among 3222 patients, the median age was 49 (range 22 to 74 years; 6% ≥ 65 years). Disease characteristics included 54% ER+ and/or PR+ and 71% node positive. Prior to randomization, all patients underwent primary surgery for breast cancer.

The results for DFS for the integrated analysis of NSABP B31 and NCCTG N9831, HERA, and BCIRG006 and OS results for the integrated analysis of NSABP B31 and NCCTG N9831, and HERA are presented in Table 9. For NSABP B31 and NCCTG N9831, the duration of DFS following a median follow-up of 2.0 years in the AC→TH arm is presented in Figure 4, and the duration of OS after a median follow-up of 8.3 years in the AC→TH arm is presented in Figure 5. The duration of DFS for BCIRG006 is presented in Figure 6. For NSABP B31 and NCCTG N9831, the OS hazard ratio was 0.64 (95% CI: 0.55, 0.74). At 8.3 years of median follow up [AC→TH], the survival rate was estimated to be 86.9% in the AC→TH arm and 79.4% in the AC→T arm. The final OS analysis results from NSABP B31 and NCCTG N9831 indicate that OS benefit by age, hormone receptor status, number of positive lymph nodes, tumor size and grade, and surgery/radiation therapy was consistent with the treatment effect in the overall population. In patients ≤ 50 years of age (n = 2197), the OS hazard ratio was 0.65 (95% CI: 0.52, 0.81) and in patients > 50 years of age (n = 1866), the OS hazard ratio was 0.63 (95% CI: 0.51, 0.78). In the subgroup of patients with hormone receptor-positive disease (ER-positive and/or PR-positive) (n = 2223), the hazard ratio for OS was 0.63 (95% CI: 0.51, 0.78). In the subgroup of patients with hormone receptor-negative disease (ER-negative and PR-negative) (n = 1830), the hazard ratio for OS was 0.64 (95% CI: 0.52, 0.80). In the subgroup of patients with tumor size ≤ 2 cm (n = 1604), the hazard ratio for OS was 0.52 (95% CI: 0.39, 0.71). In the subgroup of patients with tumor size > 2 cm (n = 2448), the hazard ratio for OS was 0.67 (95% CI: 0.56, 0.80).

Table 9: Efficacy Results from Adjuvant Treatment of Breast Cancer (NSABP B31 and NCCTG N9831, HERA, and BCIRG006)
 | DFS events | DFS Hazard ratio (95% CI) p-value | Deaths (OS events) | OS Hazard ratio p-value
NSABP B31 and NCCTG N9831 [CI = confidence interval]
AC→TH (n = 1872) [†] (n = 2031) [‡] | 133 | 0.48 [§] (0.39, 0.59) p< 0.0001 [¶] | 289 | 0.64 (0.55, 0.74) p< 0.0001
AC→T (n = 1880) (n = 2032) | 261 |  | 418
HERA [#]
Chemo→Trastuzumab (n = 1693) | 127 | 0.54 (0.44, 0.67) p< 0.0001 [Þ] | 31 | 0.75 p = NS [ß]
Chemo→Observation (n = 1693) | 219 |  | 40
BCIRG006
TCH (n = 1075) | 134 | 0.67 (0.54 to 0.84) p=0.0006 [à] | 56
AC→TH (n = 1074) | 121 | 0.60 (0.48 to 0.76) p< 0.0001 [è] | 49
AC→T (n = 1073) | 180 |  | 80

Figure 4: Duration of Disease-Free Survival in Patients with Adjuvant Treatment of Breast Cancer (NSABP B31 and NCCTG N9831)

Figure 5: Overall Survival in Patients with Adjuvant Treatment of Breast Cancer (NSABP B31 and NCCTG N9831)

Figure 6: Disease-Free Survival in Patients with Adjuvant Treatment of Breast Cancer (BCIRG006)

Exploratory analyses of DFS as a function of HER2 overexpression or gene amplification were conducted for patients in NCCTG N9831 and HERA, where central laboratory testing data were available. The results are shown in Table 10. The number of events in NCCTG N9831 was small with the exception of the IHC 3+/FISH+ subgroup, which constituted 81% of those with data. Definitive conclusions cannot be drawn regarding efficacy within other subgroups due to the small number of events. The number of events in HERA was adequate to demonstrate significant effects on DFS in the IHC 3+/FISH unknown and the FISH+/IHC unknown subgroups.

Table 10: DFS in NCCTG N9831 and HERA for Patients with HER2 Overexpression or Amplification
 | NCCTG N9831 |  | HERA [Median follow-up duration of 12.6 months in the one-year trastuzumab treatment arm.]
HER2 Assay Result [IHC by HercepTest, FISH by PathVysion (HER2/CEP17 ratio ≥ 2.0) as performed at a central laboratory.] | Number of Patients | Hazard Ratio DFS (95% CI) | Number of Patients | Hazard Ratio DFS (95% CI)
IHC 3+
FISH (+) | 1170 | 0.42 (0.27, 0.64) | 91 | 0.56 (0.13, 2.50)
FISH (-) | 51 | 0.71 (0.04, 11.79) | 8 | -
FISH Unknown | 51 | 0.69 (0.09, 5.14) | 2258 | 0.53 (0.41, 0.69)
IHC < 3+ / FISH (+) | 174 | 1.01 (0.18, 5.65) | 299 [All cases in this category in HERA were IHC 2+.] | 0.53 (0.20, 1.42)
IHC unknown / FISH (+) | - | - | 724 | 0.59 (0.38, 0.93)

14.2 Metastatic Breast Cancer

The safety and efficacy of trastuzumab in treatment of women with metastatic breast cancer were studied in a randomized, controlled clinical trial in combination with chemotherapy (H0648g, n = 469 patients) and an open-label, single agent clinical trial (H0649g, n = 222 patients). Both trials studied patients with metastatic breast cancer whose tumors overexpress the HER2 protein. Patients were eligible if they had 2 or 3 levels of overexpression (based on a 0 to 3 scale) by immunohistochemical assessment of tumor tissue performed by a central testing lab.

Previously Untreated Metastatic Breast Cancer (H0648g)

H0648g was a multicenter, randomized, open-label clinical trial conducted in 469 women with metastatic breast cancer who had not been previously treated with chemotherapy for metastatic disease. Tumor specimens were tested by IHC (Clinical Trial Assay, CTA) and scored as 0, 1+, 2+, or 3+, with 3+ indicating the strongest positivity. Only patients with 2+ or 3+ positive tumors were eligible (about 33% of those screened). Patients were randomized to receive chemotherapy alone or in combination with trastuzumab given intravenously as a 4 mg/kg loading dose followed by weekly doses of trastuzumab at 2 mg/kg. For those who had received prior anthracycline therapy in the adjuvant setting, chemotherapy consisted of paclitaxel (175 mg/m^2 over 3 hours every 21 days for at least six cycles); for all other patients, chemotherapy consisted of anthracycline plus cyclophosphamide (AC: doxorubicin 60 mg/m^2 or epirubicin 75 mg/m^2 plus 600 mg/m^2 cyclophosphamide every 21 days for six cycles). Sixty-five percent of patients randomized to receive chemotherapy alone in this study received trastuzumab at the time of disease progression as part of a separate extension study.

Based upon the determination by an independent Response Evaluation Committee, the patients randomized to trastuzumab and chemotherapy experienced a significantly longer median time to disease progression (TTP), a higher overall response rate (ORR), and a longer median duration of response (DoR), as compared with patients randomized to chemotherapy alone. Patients randomized to trastuzumab and chemotherapy also had a longer median overall survival (OS) (see Table 11). These treatment effects were observed both in patients who received trastuzumab plus paclitaxel and in those who received trastuzumab plus AC; however, the magnitude of the effects was greater in the paclitaxel subgroup.

Table 11: H0648g: Efficacy Results in First-Line Treatment for Metastatic Breast Cancer
 | Combined Results |  | Paclitaxel Subgroup |  | AC [AC = Anthracycline (doxorubicin or epirubicin) and cyclophosphamide] Subgroup
 | Trastuzumab + All Chemotherapy (n = 235) | All Chemo-therapy (n = 234) | Trastuzumab + Paclitaxel (n = 92) | Paclitaxel (n = 96) | Trastuzumab + AC (n = 143) | AC (n = 138)
Time to Disease Progression (TTP)
Median (months) | 7.2 | 4.5 | 6.7 | 2.5 | 7.6 | 5.7
95% CI | 7, 8 | 4, 5 | 5, 10 | 2, 4 | 7, 9 | 5, 7
p-value | < 0.0001 |  | < 0.0001 |  | 0.002
Overall Response Rate (ORR)
Events (n) | 45 | 29 | 38 | 15 | 50 | 38
95% CI | 39, 51 | 23, 35 | 28, 48 | 8, 22 | 42, 58 | 30, 46
p-value [Χ^2-test] | < 0.001 |  | < 0.001 |  | 0.10
Duration of Response (DoR)
Median (months) [Assessed by an independent Response Evaluation Committee] | 8.3 | 5.8 | 8.3 | 4.3 | 8.4 | 6.4
25%, 75% Quartile | 6, 15 | 4, 8 | 5, 11 | 4, 7 | 6, 15 | 4, 8
Overall Sruvival (OS)
Median (months) [Kaplan-Meier Estimate] | 25.1 | 20.3 | 22.1 | 18.4 | 26.8 | 21.4
95% CI | 22, 30 | 17, 24 | 17, 29 | 13, 24 | 23, 33 | 18, 27
p-value [log-rank test] | 0.05 |  | 0.17 |  | 0.16

Data from H0648g suggest that the beneficial treatment effects were largely limited to patients with the highest level of HER2 protein overexpression (3+) (see Table 12).

Table 12: Treatment Effects in H0648g as a Function of HER2 Overexpression or Amplification
HER2 Assay Result | Number of Patients (N) | Relative Risk [The relative risk represents the risk of progression or death in the trastuzumab plus chemotherapy arm versus the chemotherapy arm.] for Time to Disease Progression (95% CI) | Relative Risk for Mortality (95% CI)
CTA 2+ or 3+ | 469 | 0.49 (0.40, 0.61) | 0.80 (0.64, 1.00)
FISH (+) [FISH testing results were available for 451 of the 469 patients enrolled on study.] | 325 | 0.44 (0.34, 0.57) | 0.70 (0.53, 0.91)
FISH (-) | 126 | 0.62 (0.42, 0.94) | 1.06 (0.70, 1.63)
CTA 2+ | 120 | 0.76 (0.50, 1.15) | 1.26 (0.82, 1.94)
FISH (+) | 32 | 0.54 (0.21, 1.35) | 1.31 (0.53, 3.27)
FISH (-) | 83 | 0.77 (0.48, 1.25) | 1.11 (0.68, 1.82)
CTA 3+ | 349 | 0.42 (0.33, 0.54) | 0.70 (0.51, 0.90)
FISH (+) | 293 | 0.42 (0.32, 0.55) | 0.67 (0.51, 0.89)
FISH (-) | 43 | 0.43 (0.20, 0.94) | 0.88 (0.39, 1.98)

Previously Treated Metastatic Breast Cancer (H0649g)

Trastuzumab was studied as a single agent in a multicenter, open-label, single-arm clinical trial (H0649g) in patients with HER2 overexpressing metastatic breast cancer who had relapsed following one or two prior chemotherapy regimens for metastatic disease. Of 222 patients enrolled, 66% had received prior adjuvant chemotherapy, 68% had received two prior chemotherapy regimens for metastatic disease, and 25% had received prior myeloablative treatment with hematopoietic rescue. Patients were treated with a loading dose of 4 mg/kg IV followed by weekly doses of trastuzumab at 2 mg/kg IV.

The ORR (complete response + partial response), as determined by an independent Response Evaluation Committee, was 14%, with a 2% complete response rate and a 12% partial response rate. Complete responses were observed only in patients with disease limited to skin and lymph nodes. The overall response rate in patients whose tumors tested as CTA 3+ was 18% while in those that tested as CTA 2+, it was 6%.

14.3 Metastatic Gastric Cancer

The safety and efficacy of trastuzumab in combination with cisplatin and a fluoropyrimidine (capecitabine or 5-fluorouracil) were studied in patients previously untreated for metastatic gastric or gastroesophageal junction adenocarcinoma (ToGA). In this open-label, multi-center trial, 594 patients were randomized 1:1 to trastuzumab in combination with cisplatin and a fluoropyrimidine (FC+H) or chemotherapy alone (FC). Randomization was stratified by extent of disease (metastatic vs. locally advanced), primary site (gastric vs. gastroesophageal junction), tumor measurability (yes vs. no), ECOG performance status (0, 1 vs. 2), and fluoropyrimidine (capecitabine vs. 5-fluorouracil). All patients were either HER2 gene amplified (FISH+) or HER2 overexpressing (IHC 3+). Patients were also required to have adequate cardiac function (e.g., LVEF > 50%).

On the trastuzumab-containing arm, trastuzumab was administered as an IV infusion at an initial dose of 8 mg/kg followed by 6 mg/kg every 3 weeks until disease progression. On both study arms, cisplatin was administered at a dose of 80 mg/m^2 Day 1 every 3 weeks for 6 cycles as a 2 hour IV infusion. On both study arms, capecitabine was administered at 1000 mg/m^2 dose orally twice daily (total daily dose 2000 mg/m^2) for 14 days of each 21 day cycle for 6 cycles. Alternatively, continuous intravenous infusion (CIV) 5-fluorouracil was administered at a dose of 800 mg/m^2/day from Day 1 through Day 5 every three weeks for 6 cycles.

The median age of the study population was 60 years (range: 21 to 83); 76% were male; 53% were Asian, 38% Caucasian, 5% Hispanic, 5% other racial/ethnic groups; 91% had ECOG PS of 0 or 1; 82% had primary gastric cancer and 18% had primary gastroesophageal adenocarcinoma. Of these patients, 23% had undergone prior gastrectomy, 7% had received prior neoadjuvant and/or adjuvant therapy, and 2% had received prior radiotherapy.

The main outcome measure of ToGA was overall survival (OS), analyzed by the unstratified log-rank test. The final OS analysis based on 351 deaths was statistically significant (nominal significance level of 0.0193). An updated OS analysis was conducted at one year after the final analysis. The efficacy results of both the final and the updated analyses are summarized in Table 13 and Figure 7.

Table 13: Overall Survival in ToGA (ITT Population)
 | FC + Trastuzumab Arm N = 298 | FC [FC = capecitabine vs. 5-fluorouracil] Arm N = 296
Overall Survival (interim analysis)
N (%) | 167 (56.0%) | 184 (62.2%)
Median (months) | 13.5 | 11.0
95% CI | (11.7, 15.7) | (9.4, 12.5)
Hazard Ratio | 0.73
95% CI | (0.60, 0.91)
p value [Two sided p-value comparing with the nominal significance level of 0.0193] | 0.0038
Overall Survival (updated)
N (%) | 221 (74.2%) | 227 (76.7%)
Median (months) | 13.1 | 11.7
95% CI | (11.9, 15.1) | (10.3, 13.0)
Hazard Ratio | 0.80
95% CI | (0.67, 0.97)

Figure 7: Updated Overall Survival in Patients with Metastatic Gastric Cancer (ToGA)

An exploratory analysis of OS in patients based on HER2 gene amplification (FISH) and protein overexpression (IHC) testing is summarized in Table 14.

Table 14: Exploratory Analyses by HER2 Status Using Updated Overall Survival Results
 | FC (N = 296) [Two patients on the FC arm who were FISH+ but IHC status unknown were excluded from the exploratory subgroup analyses.] | FC + H (N = 298) [Five patients on the trastuzumab-containing arm who were FISH+, but IHC status unknown were excluded from the exploratory subgroup analyses.]
FISH+ / IHC 0, 1+ subgroup (N=133)
No. Deaths / n (%) | 57/71 (80%) | 56/62 (90%)
Median OS Duration (mos.) | 8.8 | 8.3
95% CI (mos.) | (6.4, 11.7) | (6.2, 10.7)
Hazard ratio (95% CI) | 1.33 (0.92, 1.92)
FISH+ / IHC2+ subgroup (N=160)
No. Deaths / n (%) | 65/80 (81%) | 64/80 (80%)
Median OS Duration (mos.) | 10.8 | 12.3
95% CI (mos.) | (6.8, 12.8) | (9.5, 15.7)
Hazard ratio (95% CI) | 0.78 (0.55, 1.10)
FISH+ or FISH- / IHC3+ [Includes 6 patients on chemotherapy arm, 10 patients on trastuzumab arm with FISH–, IHC3+ and 8 patients on chemotherapy arm, 8 patients on trastuzumab arm with FISH status unknown, IHC 3+.] subgroup (N=294)
No. Deaths / n (%) | 104/143 (73%) | 96/151 (64%)
Median OS Duration (mos.) | 13.2 | 18.0
95% CI (mos.) | (11.5, 15.2) | (15.5, 21.2)
Hazard ratio (95% CI) | 0.66 (0.50, 0.87)

16 HOW SUPPLIED/STORAGE AND HANDLING

420 mg Multiple-dose vial NDC 63459-305-47

HERZUMA (trastuzumab-pkrb) for Injection 420 mg/vial is supplied in a multiple-dose vial as a white to pale yellow lyophilized sterile powder, under vacuum. Each carton contains one multiple-dose vial (420 mg/vial) of HERZUMA and one vial (20 mL) of Bacteriostatic Water for Injection (BWFI), USP, containing 1.1% benzyl alcohol as a preservative.

150 mg Single-dose vial NDC 63459-303-43

HERZUMA (trastuzumab-pkrb) for Injection 150 mg/vial is supplied in a single-dose vial as a white to pale yellow lyophilized sterile powder, under vacuum. Each carton contains one single-dose vial (150 mg/vial) of HERZUMA.

Store HERZUMA vials in the refrigerator at 2°C to 8°C (36°F to 46°F) until time of reconstitution.

17 PATIENT COUNSELING INFORMATION

Cardiomyopathy

- Advise patients to contact a health care professional immediately for any of the following: new onset or worsening shortness of breath, cough, swelling of the ankles/legs, swelling of the face, palpitations, weight gain of more than 5 pounds in 24 hours, dizziness or loss of consciousness [see Boxed Warning: Cardiomyopathy].

Embryo-Fetal Toxicity

- Advise pregnant women and females of reproductive potential that HERZUMA exposure during pregnancy or within 7 months prior to conception can result in fetal harm. Advise female patients to contact their healthcare provider with a known or suspected pregnancy [see Use in Specific Populations (8.1)].
- Advise females of reproductive potential to use effective contraception during treatment and for 7 months following the last dose of HERZUMA [see Use in Specific Populations (8.3)].

Manufactured by:

CELLTRION, Inc.

23, Academy-ro,
Yeonsu-gu, Incheon
22014, Republic of Korea
U.S. License No. 1996

HERZUMA® is a registered trademark of CELLTRION, Inc.

Marketed by:

Teva Pharmaceuticals USA, Inc.

North Wales, PA 19454

PRINCIPAL DISPLAY PANEL - Kit Carton Label

NDC 63459-305-47

Rx only
Multiple-dose vial

Herzuma®
(trastuzumab-pkrb)
For Injection

420 mg/vial

For Intravenous Infusion Only.
Reconstitution and dilution required (see insert).
No preservative
KEEP REFRIGERATED

teva

PRINCIPAL DISPLAY PANEL - 150 mg Vial Label

NDC 63459-303-43

Rx only
Single-dose vial

Herzuma®
(trastuzumab-pkrb)
For Injection

150 mg/vial

For Intravenous Infusion Only.
Reconstitution and dilution required (see insert).
No preservative
KEEP REFRIGERATED

teva